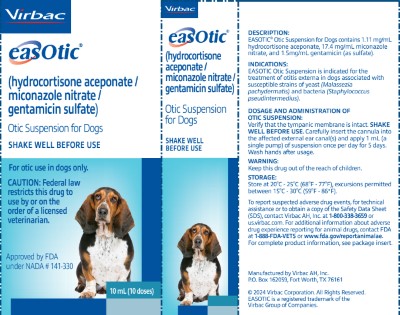 DRUG LABEL: EASOTIC
NDC: 51311-360 | Form: SUSPENSION
Manufacturer: Virbac AH, Inc.
Category: animal | Type: PRESCRIPTION ANIMAL DRUG LABEL
Date: 20240731

ACTIVE INGREDIENTS: HYDROCORTISONE ACEPONATE 1.11 mg/1 mL; MICONAZOLE NITRATE 17.4 mg/1 mL; GENTAMICIN 1.5 mg/1 mL

EASOTIC® (hydrocortisone aceponate, miconazole nitrate, gentamicin sulfate) Otic Suspension for Dogs

STATEMENT OF IDENTITY

Anti-inflammatory, antifungal, and antibacterial

Rx

For Otic Use in Dogs Only

CAUTION

Federal law restricts this drug to use by or on the order of a licensed veterinarian.

DESCRIPTION

EASOTIC® Otic Suspension contains 1.11 mg/mL hydrocortisone aceponate, 17.4 mg/mL miconazole nitrate and 1.5 mg/mL gentamicin (as sulfate). The inactive ingredient is a semi-liquid petroleum jelly.

INDICATIONS

EASOTIC Otic Suspension is indicated for the treatment of otitis externa in dogs associated with susceptible strains of yeast (Malassezia pachydermatis) and bacteria (Staphylococcus pseudintermedius).

DOSAGE AND ADMINSTRATION

Verify that the tympanic membrane is intact. Shake well before each use.

Priming the canister: Prior to the first use of the dosing container, press firmly on the pump several times, ensuring the pump goes all the way down, until the nozzle (cannula) fills with a full dose of product. Once the nozzle is filled with product it is ready for administration.

Carefully insert the cannula into the aected external ear canal(s) and apply 1 mL (a single pump) of EASOTIC Otic Suspension once per day for 5 days. Wash hands aer usage.

CONTRAINDICATIONS

Do not use in dogs with known tympanic membrane perforation.

EASOTIC Otic Suspension is contraindicated in dogs with known or suspected hypersensitivity to corticosteroids, imidazole antifungals, or aminoglycoside antibiotics.

WARNINGS

Human Warnings: Not for use in humans. Keep this and all drugs out of reach of children. In case of accidental skin contact, wash area thoroughly with soap and water. Avoid contact with eyes.

Humans with known or suspected hypersensitivity to hydrocortisone, aminoglycoside antibiotics, or azole antifungals should not handle this product.

In case of accidental ingestion by humans, contact a physician immediately. Physicians may contact a Poison Control Center for advice concerning cases of ingestion by humans.

Animal Warnings: As a class, aminoglycoside antibiotics are associated with ototoxicity, vestibular dysfunction and renal toxicity. The use of EASOTIC Otic Suspension in a dog with a damaged tympanic membrane can result in damage to the structures of the ear associated with hearing and balance or in transmission of the infection to the middle or inner ear. Immediately discontinue use of EASOTIC Otic
Suspension if hearing loss or signs of vestibular dysfunction are observed during treatment (see ADVERSE REACTIONS).

PRECAUTIONS

Do not administer orally.

Concurrent administration of potentially ototoxic drugs should be avoided. Use with caution in dogs with impaired hepatic or renal function (see ANIMAL SAFETY).

Long-term use of topical otic corticosteroids has been associated with adrenocortical suppression and iatrogenic hyperadrenocorticism in dogs (see ANIMAL SAFETY).

The safe use of EASOTIC Otic Suspension in dogs used for breeding purposes, during pregnancy, or in lactating bitches, has not been evaluated.

ADVERSE REACTIONS

In a field study conducted in the United States (see EFFECTIVENESS), there were no adverse reactions reported in 145 dogs administered EASOTIC (hydrocortisone aceponate, miconazole nitrate, gentamicin sulfate) Otic Suspension for Dogs.

In foreign market experience, reports of hearing loss and application site erythema have been received. In most reported cases, the hearing loss and erythema were transient and resolved with discontinuation of EASOTIC Otic Suspension.

CONTACT INFORMATION
To report suspected adverse drug events, for technical assistance or to obtain a copy of the Safety Data Sheet (SDS), contact Virbac AH, Inc. at 1-800-338-3659 or us.virbac.com. For additional information about adverse drug experience reporting for animal drugs, contact FDA at 1-888-FDA-VETS or www.fda.gov/reportanimalae.

PHARMACOLOGY

Hydrocortisone aceponate is a glucocorticoid with anti-inflammatory effects. Miconazole nitrate is an imidazole antifungal. Gentamicin sulfate is an aminoglycoside antibiotic.

In the target animal safety study, hydrocortisone aceponate, miconazole and gentamicin were shown to be systemically absorbed from the ears of healthy dogs (see ANIMAL SAFETY); increased systemic absorption may be observed in inflamed ears.

MICROBIOLOGY

The compatibility and additive effect of each of the components in EASOTIC Otic Suspension was demonstrated in a component effectiveness and non-interference study. An in vitro study of organisms collected from clinical cases of otitis externa in dogs and from dogs enrolled in the clinical effectiveness study for EASOTIC Otic Suspension determined that miconazole nitrate and gentamicin sulfate inhibit the growth of bacteria and yeast commonly associated with otitis externa in dogs. No consistent synergistic or antagonistic effect of the two antimicrobials was demonstrated. The addition of hydrocortisone aceponate to the combination did not impair antimicrobial activity to any clinically-significant extent.

In a field study (see EFFECTIVENESS), the minimum of 10 isolates from successfully treated cases was met for S. pseudintermedius and M. pachydermatis.

EFFECTIVENESS

The effectiveness of this drug was evaluated in 157 dogs with otitis externa. The study was a double-masked field study with a placebo control. One hundred four dogs were treated with EASOTIC Otic Suspension and 53 dogs were treated with the placebo control. Treatment was administered once daily for 5 consecutive days to the affected ear(s). The dogs were evaluated at 4 different intervals over the course of 1 month to determine response to therapy. The 6 clinical signs evaluated were: malodor, aural discharge, pruritus, erythema, swelling and pain. The individual clinical scores were assigned based on the severity of each sign. Success was based on clinical improvement at Day 28 ± 2 days. The success rates of the 2 groups were significantly different (p=0.0179); 68.5% of dogs administered EASOTIC Otic Suspension were successfully treated, compared to 21.8% of the dogs in the placebo control group.

ANIMAL SAFETY

In the target animal safety study, EASOTIC Otic Suspension was administered at 0X, 1X, 3X and 5X the recommended dose for 15 consecutive days (3 times the recommended treatment duration) in laboratory Beagles, with 8 dogs per group. Hypersensitivity reactions in the external ear canal and inner pinnae were seen in all EASOTIC Otic Suspension groups and included mild to severe aural erythema (3X group),papules and ulceration (1X and 5X groups), otitis externa (3X and 5X groups), and otitis media (5X group). Renal tubular crystals were present in the cortex and medulla (0X, 1X, 3X, and 5X groups) and mild renal tubular basophilia and atrophy were present in one 5X group dog.Baseline cortisol values and the cortisol response to ACTH stimulation were lower in treated dogs compared to the control dogs. The ACTH stimulation test results are consistent with systemic absorption of topical corticosteroids causing suppression of the hypothalamic-pituitary-adrenal axis. Dogs in the 3X and 5X groups demonstrated elevations in AST and ALP, while dogs in the 1X, 3X, and 5X groups had elevated cholesterol,total protein, and albumin levels. Dogs in the 3X and 5X groups also had higher liver weights and greater food consumption.

STORAGE INFORMATION

Store at temperatures between 20oC-25oC (68oF-77oF), with excursions permitted between 15 oC-30 oC (59 oF-86 oF).

HOW SUPPLIED

EASOTIC Otic Suspension is supplied in a polyethylene canister, with a soft applicator cannula. Each canister contains ten 1 mL doses.

Made in the U.S.A.

Manufactured by:
Virbac AH, Inc.
P.O. Box 162059
Fort Worth, TX 76161 USA

Approved by FDA under NADA # 141-330
Revision Date 04/2024
© 2024 Virbac Corporation. All Rights Reserved.
EASOTIC is a registered trademark of the
Virbac Group of Companies.

09420 302076-06